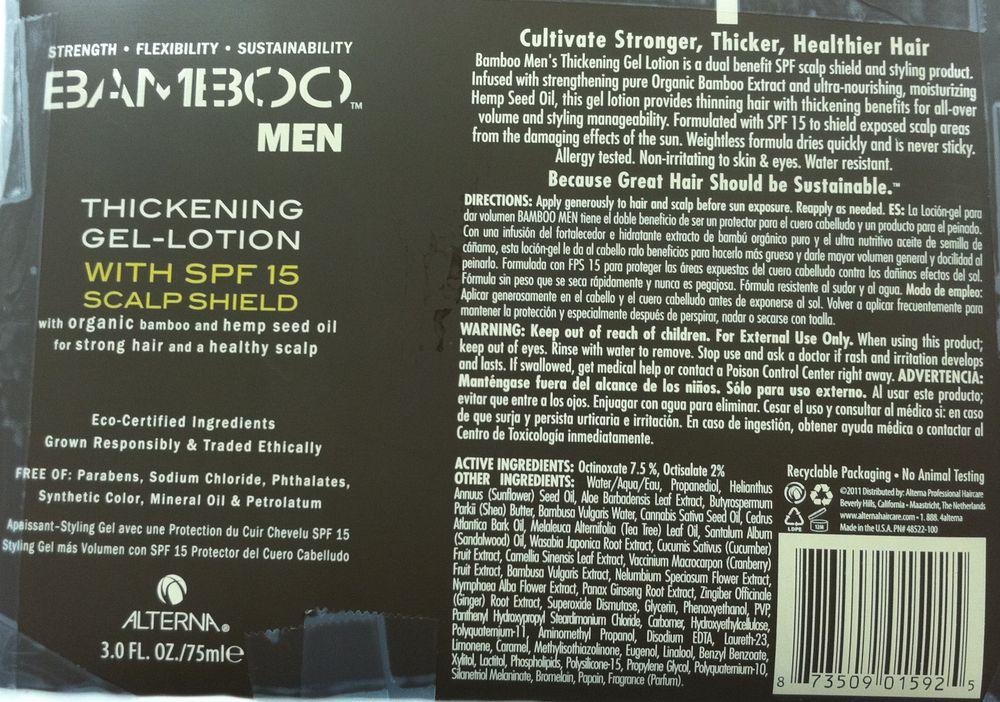 DRUG LABEL: Bamboo Mens Thickening
NDC: 53138-3012 | Form: EMULSION
Manufacturer: Cosway Company, Inc.
Category: otc | Type: HUMAN OTC DRUG LABEL
Date: 20111019

ACTIVE INGREDIENTS: Octinoxate 5.6 g/75 mL; Octisalate 1.5 g/75 mL
INACTIVE INGREDIENTS: Water; Propanediol; Sunflower Oil; Aloe Vera Leaf; Shea Butter; Bambusa Vulgaris Whole; Cannabis Sativa Seed Oil; Cedrus Atlantica Bark Oil; Tea Tree Oil; Sandalwood Oil; Eutrema Japonicum Root; Cucumber; Green Tea Leaf; Cranberry; Bambusa Vulgaris Top; Nelumbo Nucifera Flower; Nymphaea Alba Flower; Asian Ginseng; Ginger; Orgotein; Glycerin; Phenoxyethanol; Aminomethylpropanol; Edetate Disodium; Laureth-23; LIMONENE, (+/-)-; Caramel; Methylisothiazolinone; Eugenol; Linalool, (+/-)-; Benzyl Benzoate; Xylitol; Lactitol; Polysilicone-15; Propylene Glycol; Papain

Drug Facts

Active Ingredient

Octinoxate 7.5%, Octisalate 2%

Purpose

Strength, Fexibility and Sustainability

Use

Cultivate, Thicker, Healthier Hair

Bamboo Men's Thickening Gel Lotion is dual benefit SPF scalp shield and styling product. Infused with strengthening pure Organic Bamboo Extract and ultra-nourishing, moisturizing Hemp Seed Oil, this lotion provides thinning hair with thickening benefits for all-over volume and styling manageability. Formulated with SPF 15 to shield exposed scalp areas from the damaging effects of the sun. Weightless formula dries quickly and is never sticky.

Warnings

For external use only

When using this product; keep out of eyes. Rinse with water to remove. Stop use and ask a doctor if rash and irritation develops and lasts. If swallowed, get medical help or contact a Poison Control Center right away.

Keep out of reach of children.

Directions

Apply generously to hair and scalp before sun exposure. Reapply as needed.

Inactive ingredients

Inactive ingredients: Water (Aqua), Propanediol, Helianthus Annuus (Sunflower) Seed Oil, Aloe Barbadensis Leaf Extract, Butyrospermum Parkii (Shea) Butter, Bambusa Vulgaris Water, Cannabis Sativa Seed Oil, Cedrus Atlantica Bark Oil, Melaleuca Alternifolia (Tea Tree) Leaf Oil, Santalum Album (Sandalwood) Oil, Wasabi Japonica Root Extract, Cucumis Sativus (Cucumber) Fruit Extract, Camellia Sinensis Leaf Extract, Vaccinium Macrocarpon (Cranberry) Fruit Extract, Bambusa Vulgaris Extract, Nelumbium Speciosum Flower Extract, Nyphaea Alba Flower Extract, Panax Ginseng Root Extract, Zingiber Officinale (Ginger) Root Extract, Superoxide Dismutase, Glycerin, Phenoxyethanol, PVP, Panthenyl Hydroxypropyl Steardimonium Chloride, Carbomer, Hydroxyethylcellulose, Polyquaternium-11, Aminomethyl Propanol, Disodium EDTA, Laureth-23, Limonene, Caramel, Methylisothiazolinone, Eugenol, Linalool, Benzyl Benzoate, Xylitol, Lactitol, Phospholipids, Polysilicone-15, Propylene Glycol, Polyquaternium-10, Silanetriol Melaninate, Bromelain, Papai, Fragrance (Parfum)

SPL Unclassified Section

2011 Distributed by: Alterna Profesional Haircare

Beverly Hills, California Maastricht, The Netherlands

www.alternahaircare.com 1.888.4alterna Made in the USA PN# 48522-100

Package Label Principal Display Panel

Strength * Flexibility * Sustainability

Bamboo Men

Thickening Gel-Lotion with SPF15 Scalp Shield

with organic bamboo and hemp seed oil for strong hair and a healthy scalp

Eco-certified ingredients

Grown Responsibly and Traded Ethically

Free of: Parabens, Sodium Chloride, Phthalates, Synthetic Color, Mineral Oil and Petrolatum

Apaissant-Styling Gel avec une Protection du Cuir Chevelu SPF 15

Styling Gel mas Volumen con SPF 15 Protector del Cuero Cabelludo

ALTERNA

3.0 fl oz / 75 ml e